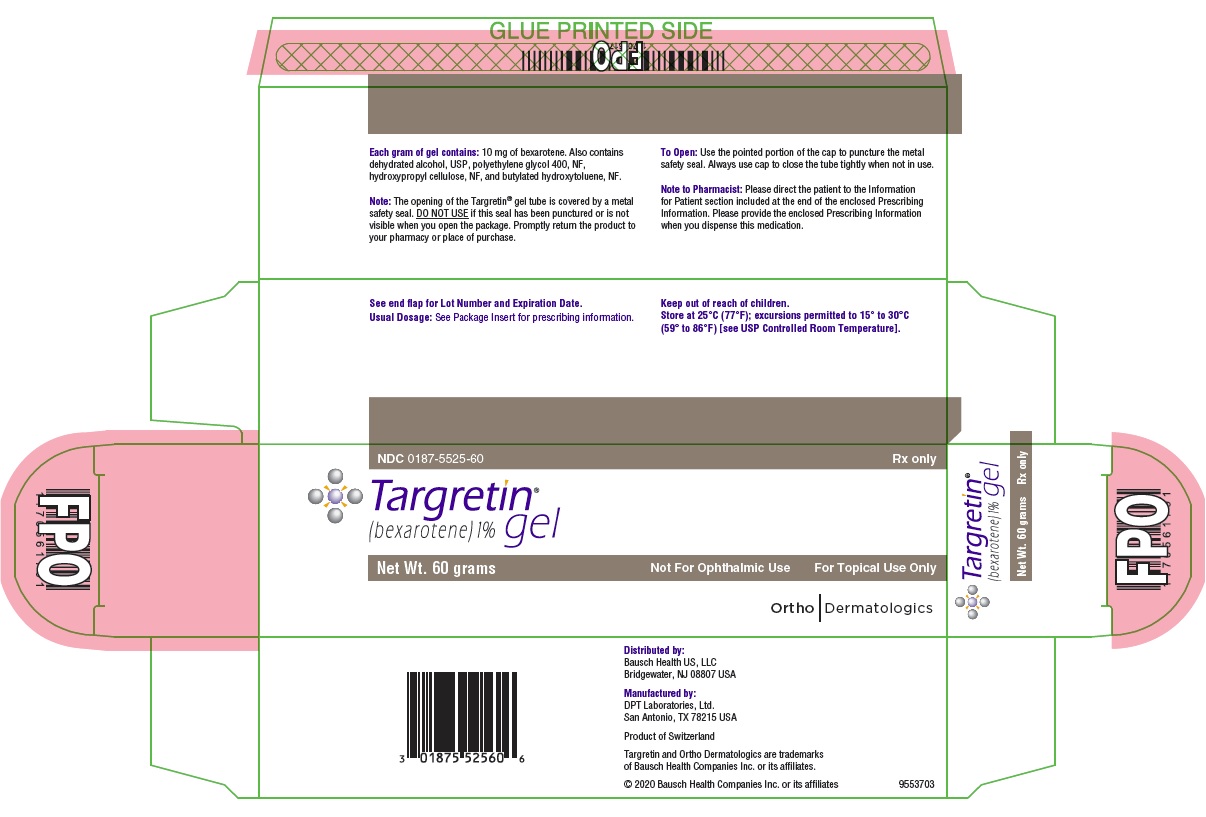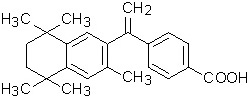 DRUG LABEL: Targretin
NDC: 0187-5525 | Form: GEL
Manufacturer: Bausch Health US, LLC
Category: prescription | Type: HUMAN PRESCRIPTION DRUG LABEL
Date: 20200203

ACTIVE INGREDIENTS: BEXAROTENE 1 g/100 g
INACTIVE INGREDIENTS: ALCOHOL; POLYETHYLENE GLYCOL 400; HYDROXYPROPYL CELLULOSE, UNSPECIFIED; BUTYLATED HYDROXYTOLUENE

Targretin®
(bexarotene) gel 1%
Rx only

DESCRIPTION

Targretin® (bexarotene) gel 1% contains bexarotene and is intended for topical application only. Bexarotene is a member of a subclass of retinoids that selectively activate retinoid X receptors (RXRs). These retinoid receptors have biologic activity distinct from that of retinoic acid receptors (RARs).

The chemical name is 4-[1-(5,6,7,8-tetrahydro-3,5,5,8,8-pentamethyl-2-naphthalenyl)ethenyl] benzoic acid, and the structural formula is as follows:

Bexarotene is an off-white to white powder with a molecular weight of 348.48 and a molecular formula of C24H28O2. It is insoluble in water and slightly soluble in vegetable oils and ethanol, USP.

Targretin gel is a clear gelled solution containing 1.0% (w/w) bexarotene in a base of dehydrated alcohol, USP, polyethylene glycol 400, NF, hydroxypropyl cellulose, NF, and butylated hydroxytoluene, NF.

CLINICAL PHARMACOLOGY

Mechanism of Action

Bexarotene selectively binds and activates retinoid X receptor subtypes (RXRα, RXRβ, RXRγ). RXRs can form heterodimers with various receptor partners such as retinoic acid receptors (RARs), vitamin D receptor, thyroid receptor, and peroxisome proliferator activator receptors (PPARs). Once activated, these receptors function as transcription factors that regulate the expression of genes that control cellular differentiation and proliferation. Bexarotene inhibits the growth in vitro of some tumor cell lines of hematopoietic and squamous cell origin. It also induces tumor regression in vivo in some animal models. The exact mechanism of action of bexarotene in the treatment of cutaneous T-cell lymphoma (CTCL) is unknown.

Pharmacokinetics

General

Plasma concentrations of bexarotene were determined during clinical studies in patients with CTCL or following repeated single or multiple-daily dose applications of Targretin gel 1% for up to 132 weeks. Plasma bexarotene concentrations were generally less than 5 ng/mL and did not exceed 55 ng/mL. However, only two patients with very intense dosing regimens (> 40% BSA lesions and QID dosing) were sampled. Plasma bexarotene concentrations and the frequency of detecting quantifiable plasma bexarotene concentrations increased with increasing percent body surface area treated and increasing quantity of Targretin gel applied. The sporadically observed and generally low plasma bexarotene concentrations indicated that, in patients receiving doses of low to moderate intensity, there is a low potential for significant plasma concentrations following repeated application of Targretin gel. Bexarotene is highly bound (>99%) to plasma proteins. The plasma proteins to which bexarotene binds have not been elucidated, and the ability of bexarotene to displace drugs bound to plasma proteins and the ability of drugs to displace bexarotene binding have not been studied (see PRECAUTIONS, Protein Binding). The uptake of bexarotene by organs or tissues has not been evaluated.

Metabolism

Four bexarotene metabolites have been identified in plasma following oral administration of bexarotene: 6- and 7-hydroxy-bexarotene and 6- and 7-oxo-bexarotene. In vitro studies suggest that cytochrome P450 3A4 is the major cytochrome P450 responsible for formation of the oxidative metabolites and that the oxidative metabolites may be glucuronidated. The oxidative metabolites are active in in vitro assays of retinoid receptor activation, but the relative contribution of the parent and any metabolites to the efficacy and safety of Targretin gel is unknown.

Elimination

The renal elimination of bexarotene and its metabolites was examined in patients with Type 2 diabetes mellitus following oral administration of bexarotene. Neither bexarotene nor its metabolites were excreted in urine in appreciable amounts.

Special Populations

Elderly, Gender, Race: Because of a large number of immeasurable plasma concentrations (< 1ng/mL), any potential pharmacokinetic differences between Special Populations could not be assessed.

Pediatric: Studies to evaluate bexarotene pharmacokinetics in the pediatric population have not been conducted (see PRECAUTIONS, Pediatric Use).

Renal Insufficiency: No formal studies have been conducted with Targretin gel in patients with renal insufficiency. Urinary elimination of bexarotene and its known metabolites is a minor excretory pathway (<1% of an orally administered dose), but because renal insufficiency can result in significant protein binding changes, pharmacokinetics may be altered in patients with renal insufficiency (see PRECAUTIONS, Renal Insufficiency).

Hepatic Insufficiency: No specific studies have been conducted with Targretin gel in patients with hepatic insufficiency. Because less than 1% of the dose of oral bexarotene is excreted in the urine unchanged and there is in vitro evidence of extensive hepatic contribution to bexarotene elimination, hepatic impairment would be expected to lead to greatly decreased clearance (see PRECAUTIONS, Hepatic Insufficiency).

Drug-Drug Interactions

No formal studies to evaluate drug interactions with bexarotene or Targretin gel have been conducted. Bexarotene oxidative metabolites appear to be formed through cytochrome P450 3A4. Drugs that affect levels or activity of cytochrome P450 3A4 may potentially affect the disposition of bexarotene. Concomitant gemfibrozil was associated with increased bexarotene concentrations following oral administration of bexarotene.

Clinical Studies

Targretin gel was evaluated for the treatment of patients with early stage (Stage IA-IIA) CTCL in one multicenter, open-label, clinical trial as well as in a Phase I-II program (dose-seeking trials with different response criteria than the multicenter trial). These clinical studies enrolled a total of 117 patients.

In the multicenter, open-label clinical trial, Targretin gel was evaluated for the treatment of patients with early stage CTCL who were refractory to, intolerant to, or reached a response plateau for at least six months on at least two prior therapies. The study was conducted in the U.S., Canada, Europe, and Australia and enrolled a total of 50 patients; 46% of these patients were male, 80% were Caucasian, and the median age was 64 years (range 13 to 85).

Targretin gel was also evaluated for the treatment of patients with CTCL in a U.S. Phase I-II program involving patients with early stage CTCL. This program enrolled a total of 67 patients; 55% of these patients were male, 85% were Caucasian, and the median age was 61 years (range 30 to 87).

In the multicenter, open-label clinical trial, considering prior systemic, irradiation, and topical treatments, patients had been exposed to a median of three prior therapies (range 2-7). All patients failed at least two treatments; the majority (68%) of patients were either refractory to two or more therapies or were refractory to one therapy and intolerant to at least one therapy.

Patients were treated with Targretin gel 1% for a planned 16-week period with an option to continue provided that no unacceptable toxicity was occurring.

Tumor response was assessed in the multicenter study by observation of up to five baseline-defined index lesions using a Composite Assessment of Index Lesion Disease Severity (CA). This endpoint was based on a summation of the grades, for all index lesions, of erythema, scaling, plaque elevation, hypopigmentation or hyperpigmentation, and area of involvement. New cutaneous lesions or tumors and extracutaneous disease manifestations were not considered in response or disease progression assessments.

All tumor responses required confirmation over at least two assessments separated by at least four weeks. A partial response was defined as an improvement of at least 50% in the index lesions. A complete clinical response required complete disappearance of the index lesions, but did not require confirmation by biopsy.

Targretin gel produced an overall response rate of 26% (13/50) with a corresponding exact 95% confidence interval from 14.6% to 40.3% by the Composite Assessment of Index Lesion Severity. For the Stage IA and IB patients, the response rate was 28% (13/47) with a corresponding exact 95% confidence interval from 15.6% to 42.6%. For the Stage II patients the response rate was 0% (0/3). Two percent of patients (1/50) had a clinical complete response. The median time to best response on the Composite Assessment of Index Lesion Severity (n=13) was 85 days (range: 36-154).

The rate of relapse in responding patients by the Composite Assessment of Index Lesion Severity was 23% (3/13) over a median observation period of 149 days (range 56-342). Fourteen patients developed new lesions in untreated areas (14/50; 28%). Four patients developed clinically abnormal lymph nodes (≥1 cm diam) (4/50; 8%). One patient developed a cutaneous tumor (1/50; 2%).

The Phase I-II program (dose-seeking trials with different response criteria than the multicenter trial) was supportive of the multicenter study results.

INDICATIONS AND USAGE

Targretin (bexarotene) gel 1% is indicated for the topical treatment of cutaneous lesions in patients with CTCL (Stage IA and IB) who have refractory or persistent disease after other therapies or who have not tolerated other therapies.

CONTRAINDICATIONS

Targretin gel 1% is contraindicated in patients with a known hypersensitivity to bexarotene or other components of the product.

Pregnancy

Targretin gel 1% may cause fetal harm when administered to a pregnant woman.

Targretin gel must not be given to a pregnant woman or a woman who intends to become pregnant. If a woman becomes pregnant while taking Targretin gel, Targretin gel must be stopped immediately and the woman given appropriate counseling.

Bexarotene caused malformations when administered orally to pregnant rats during days 7-17 of gestation. Developmental abnormalities included incomplete ossification at 4 mg/kg/day and cleft palate, depressed eye bulge/microphthalmia, and small ears at 16 mg/kg/day. At doses greater than 10 mg/kg/day, bexarotene caused developmental mortality. The no-effect oral dose in rats was 1 mg/kg/day. Plasma bexarotene concentrations in patients with CTCL applying Targretin gel 1% were generally less than one hundredth the Cmax associated with dysmorphogenesis in rats, although some patients had Cmax levels that were approximately one eighth the concentration associated with dysmorphogenesis in rats.

Women of child-bearing potential should be advised to avoid becoming pregnant when Targretin gel is used. The possibility that a woman of child-bearing potential is pregnant at the time therapy is instituted should be considered. A negative pregnancy test (e.g., serum beta-human chorionic gonadotropin, beta-HCG) with a sensitivity of at least 50 mIU/L should be obtained within one week prior to Targretin gel therapy, and the pregnancy test must be repeated at monthly intervals while the patient remains on Targretin gel. Effective contraception must be used for one month prior to the initiation of therapy, during therapy and for at least one month following discontinuation of therapy; it is recommended that two reliable forms of contraception be used simultaneously unless abstinence is the chosen method. Male patients with sexual partners who are pregnant, possibly pregnant, or who could become pregnant must use condoms during sexual intercourse while applying Targretin gel and for at least one month after the last dose of drug. Targretin gel therapy should be initiated on the second or third day of a normal menstrual period. No more than a one month supply of Targretin gel should be given to the patient so that the results of pregnancy testing can be assessed and counseling regarding avoidance of pregnancy and birth defects can be reinforced.

PRECAUTIONS

Pregnancy: See CONTRAINDICATIONS.

GENERAL PRECAUTIONS

General: Targretin gel should be used with caution in patients with a known hypersensitivity to other retinoids. No clinical instances of cross-reactivity have been noted.

Vitamin A Supplementation: In clinical studies, patients were advised to limit vitamin A intake to ≤15,000 IU/day. Because of the relationship of bexarotene to vitamin A, patients should be advised to limit vitamin A supplements to avoid potential additive toxic effects.

Photosensitivity: Retinoids as a class have been associated with photosensitivity. In vitro assays indicate that bexarotene is a potential photosensitizing agent. There were no reports of photosensitivity in patients in the clinical studies. Patients should be advised to minimize exposure to sunlight and artificial ultraviolet light during the use of Targretin gel.

Information for Patients

Please see accompanying “Patient’s Instructions for Use”.

Drug-Drug Interactions

Patients who are applying Targretin gel should not concurrently use products that contain DEET (N,N-diethyl-m-toluamide), a common component of insect repellent products. An animal toxicology study showed increased DEET toxicity when DEET was included as part of the formulation.

No formal studies to evaluate drug interactions with bexarotene have been conducted. Bexarotene oxidative metabolites appear to be formed through cytochrome P450 3A4.

On the basis of the metabolism of bexarotene by cytochrome P450 3A4, concomitant ketoconazole, itraconazole, erythromycin and grapefruit juice could increase bexarotene plasma concentrations. Similarly, based on data that gemfibrozil increases bexarotene concentrations following oral bexarotene administration, concomitant gemfibrozil could increase bexarotene plasma concentrations. However, due to the low systemic exposure to bexarotene after low to moderately intense gel regimens (see CLINICAL PHARMACOLOGY), increases that occur are unlikely to be of sufficient magnitude to result in adverse effects.

No drug interaction data are available on concomitant administration of Targretin gel and other CTCL therapies.

Renal Insufficiency

No formal studies have been conducted with Targretin gel in patients with renal insufficiency. Urinary elimination of bexarotene and its known metabolites is a minor excretory pathway for bexarotene (<1% of an orally administered dose), but because renal insufficiency can result in significant protein binding changes, and bexarotene is >99% protein bound, pharmacokinetics may be altered in patients with renal insufficiency.

Hepatic Insufficiency

No specific studies have been conducted with Targretin gel in patients with hepatic insufficiency. Because less than 1% of the dose of oral bexarotene is excreted in the urine unchanged and there is in vitro evidence of extensive hepatic contribution to bexarotene elimination, hepatic impairment would be expected to lead to greatly decreased clearance.

Protein Binding

Bexarotene is highly bound (>99%) to plasma proteins. The plasma proteins to which bexarotene binds have not been elucidated, and the ability of bexarotene to displace drugs bound to plasma proteins and the ability of drugs to displace bexarotene binding have not been studied.

Carcinogenesis, Mutagenesis, Impairment of Fertility

Long-term studies in animals to assess the carcinogenic potential of bexarotene have not been conducted. Bexarotene was not mutagenic to bacteria (Ames assay) or mammalian cells (mouse lymphoma assay). Bexarotene was not clastogenic in vivo (micronucleus test in mice). No formal fertility studies were conducted with bexarotene. Bexarotene caused testicular degeneration when oral doses of 1.5 mg/kg/day were given to dogs for 91 days.

Use in Nursing Mothers

It is not known whether bexarotene is excreted in human milk. Because many drugs are excreted in human milk and because of the potential for serious adverse reactions in nursing infants from bexarotene, a decision should be made whether to discontinue nursing or to discontinue the drug, taking into account the importance of the drug to the mother.

Pediatric Use

Safety and effectiveness in pediatric patients have not been established.

Geriatric Use

Of the total patients with CTCL in clinical studies of Targretin gel, 62% were under 65 years and 38% were 65 years or older. No overall differences in safety were observed between patients 65 years of age or older and younger patients, but greater sensitivity of some older individuals to Targretin gel cannot be ruled out. Responses to Targretin gel were observed across all age group decades, without preference for any individual age group decade.

ADVERSE REACTIONS

The safety of Targretin gel has been assessed in clinical studies of 117 patients with CTCL who received Targretin gel for up to 172 weeks. In the multicenter open-label study, 50 patients with CTCL received Targretin gel for up to 98 weeks. The mean duration of therapy for these 50 patients was 199 days. The most common adverse events reported with an incidence at the application site of at least 10% in patients with CTCL were rash, pruritus, skin disorder, and pain.

Adverse events leading to dose reduction or study drug discontinuation in at least two patients were rash, contact dermatitis, and pruritus.

Of the 49 patients (98%) who experienced any adverse event, most experienced events categorized as mild (9 patients, 18%) or moderate (27 patients, 54%). There were 12 patients (24%) who experienced at least one moderately severe adverse event. The most common moderately severe events were rash (7 patients, 14%) and pruritus (3 patients, 6%). Only one patient (2%) experienced a severe adverse event (rash).

In the patients with CTCL receiving Targretin gel, adverse events reported regardless of relationship to study drug at an incidence of ≥5% are presented in Table 1.

A similar safety profile for Targretin gel was demonstrated in the Phase I-II program. For the 67 patients enrolled in the Phase I-II program, the mean duration of treatment was 436 days (range 12-1203 days). As in the multicenter study, the most common adverse events regardless of relationship to study drug in the Phase I-II program were rash (78%), pain (40%), and pruritus (40%).

Table 1. Incidence of All Adverse Events* and Application Site Adverse Events with Incidence ≥5% for All Application Frequencies of Targretin Gel in the Multicenter CTCL Study
 | All Adverse Events | Application Site Adverse Events
COSTART 5 Body System/Preferred Term | N = 50 n (%) | N = 50 n (%)
Skin and Appendages
Contact Dermatitis^1 | 7 (14) | 4 (8)
Exfoliative Dermatitis | 3 (6) | 0
Pruritus^2 | 18 (36) | 9 (18)
Rash^3 | 36 (72) | 28 (56)
Maculopapular Rash | 3 (6) | 0
Skin Disorder (NOS)^4 | 13 (26) | 9 (18)
Sweating | 3 (6) | 0
Body as a Whole
Asthenia | 3 (6) | 0
Headache | 7 (14) | 0
Infection | 9 (18) | 0
Pain | 15 (30) | 9 (18)
Cardiovascular
Edema | 5 (10) | 0
Peripheral Edema | 3 (6) | 0
Hemic and Lymphatic
Leukopenia | 3 (6) | 0
Lymphadenopathy | 3 (6) | 0
WBC Abnormal | 3 (6) | 0
Metabolic and Nutritional
Hyperlipemia | 5 (10) | 0
Nervous
Paresthesia | 3 (6) | 3 (6)
Respiratory
Cough Increased | 3 (6) | 0
Pharyngitis | 3 (6) | 0
* Regardless of association with treatment
Includes Investigator terms such as:
^1 Contact dermatitis, irritant contact dermatitis, irritant dermatitis
^2 Pruritus, itching, itching of lesion
^3 Erythema, scaling, irritation, redness, rash, dermatitis
^4 Skin inflammation, excoriation, sticky or tacky sensation of skin; NOS = Not Otherwise Specified
To report SUSPECTED ADVERSE REACTIONS, contact Bausch Health US, LLC at 1-800-321-4576 or FDA at 1-800-FDA-1088 or www.fda.gov/medwatch.

OVERDOSAGE

Systemic toxicity following acute overdosage with topical application of Targretin gel is unlikely because of low systemic plasma levels observed with normal therapeutic doses. There is no specific antidote for overdosage.

There has been no experience with acute overdose of Targretin gel in humans. Any overdose with Targretin gel should be treated with supportive care for the signs and symptoms exhibited by the patient.

DOSAGE AND ADMINISTRATION

Targretin gel should be initially applied once every other day for the first week. The application frequency should be increased at weekly intervals to once daily, then twice daily, then three times daily and finally four times daily according to individual lesion tolerance. Generally, patients were able to maintain a dosing frequency of two to four times per day. Most responses were seen at dosing frequencies of two times per day and higher. If application site toxicity occurs, the application frequency can be reduced. Should severe irritation occur, application of drug can be temporarily discontinued for a few days until the symptoms subside. See CONTRAINDICATIONS, Pregnancy.

Sufficient gel should be applied to cover the lesion with a generous coating. The gel should be allowed to dry before covering with clothing. Because unaffected skin may become irritated, application of the gel to normal skin surrounding the lesions should be avoided. In addition, do not apply the gel near mucosal surfaces of the body.

A response may be seen as soon as four weeks after initiation of therapy but most patients require longer application. With continued application, further benefit may be attained. The longest onset time for the first response among the responders was 392 days based on the Composite Assessment of Index Lesion Severity in the multicenter study. In clinical trials, Targretin gel was applied for up to 172 weeks.

Targretin gel should be continued as long as the patient is deriving benefit.

Occlusive dressings should not be used with Targretin gel.

Targretin gel is a topical therapy and is not intended for systemic use.
Targretin gel has not been studied in combination with other CTCL therapies.

HOW SUPPLIED

Targretin gel is supplied in tubes containing 60 g (600 mg active bexarotene).

60 g tube………………………………………NDC 0187-5525-60

Store at 25°C (77°F); excursions permitted to 15° to 30°C (59° to 86°F) [see USP Controlled Room Temperature]. Avoid exposing to high temperatures and humidity after the tube is opened. Protect from light.

Distributed by: Bausch Health US, LLC
  Bridgewater, NJ 08807 USA
Manufactured by: DPT Laboratories, Ltd.
  San Antonio, TX 78215 USA

Targretin is a trademark of Bausch Health Companies Inc. or its affiliates.

© 2020 Bausch Health Companies Inc. or its affiliates

Rev. 02/2020

9553902

Patient’s Instructions for Use

Targretin® (bexarotene) 1% gel
(For Topical Use Only)

To help you get the full benefits from this medicine, you should read this leaflet carefully and ask your doctor to explain anything you do not understand.

What are the most important things I should know about Targretin® gel?

Do not use Targretin gel if you are pregnant or if you plan to become pregnant.

- Targretin gel may harm your fetus (unborn baby). You should contact your doctor immediately if you believe or suspect you are pregnant while you are using Targretin gel and until one month after you stop using Targretin gel.
- If you are capable of becoming pregnant, you must have a pregnancy test, within one week before you start Targretin gel therapy and monthly while you are using Targretin gel, confirming you are not pregnant.
- You must use effective contraception (birth control) continuously starting one month before beginning treatment with Targretin gel until one month after you stop using Targretin gel. It is recommended that two reliable forms of contraception be used together.
- If you are male and your partner is pregnant or capable of becoming pregnant, you should discuss with your doctor the precautions you should take.

What is Targretin gel?

Targretin (tar-GRET-in) gel contains bexarotene (beks-AIR-oh-teen). Targretin gel belongs to a class of medicines known as retinoids.

What are the uses for Targretin gel?

This medicine is used to treat the skin problems arising from a disease called cutaneous T-cell lymphoma, or CTCL. Your health care provider has prescribed Targretin for the topical treatment of the cutaneous T-cell lymphoma (CTCL), or mycosis fungoides (MF), lesions (sometimes referred to as patches or plaques) on your skin. Your doctor must instruct you on the proper use of Targretin gel. The following instructions will help you successfully begin and continue your treatment.

Do not use Targretin gel if you are allergic to this medicine.

Do not use Targretin gel if you are pregnant or believe you may be pregnant.

If you have any of the following conditions, make sure you have discussed them with your doctor before you start to take this medicine.

- If you are breast feeding.
- If you are allergic to retinoid medications (for example: Accutane [isotretinoin], Soriatane [acitretin], Tegison [etretinate], Vesinoid [tretinoin]).

When should you be extra careful while using Targretin gel?

- Because vitamin A in large doses may cause some side effects which are similar to those seen in patients applying Targretin gel, do not take more than the recommended daily dietary allowance of vitamin A (4000 to 5000 International Units). If you take vitamins, check the label to see how much vitamin A they contain. If you are not sure, ask your doctor or pharmacist.
- Your skin may become more sensitive to sunlight while using this medicine. Minimize exposure to sunlight and do not use a sunlamp.

WARNINGS

For external use only.

DO NOT apply the gel on or near mucosal surfaces of the body such as eyes, nostrils, mouth, lips, vagina, tip of the penis, rectum, or anus.

DO NOT use insect repellents containing DEET (N,N-diethyl-m-toluamide) or other products containing DEET while using Targretin gel.

Keep out of reach of children.

Product contains alcohol and should be kept away from open flame.

DO NOT use Targretin gel if you are pregnant or breastfeeding. Speak to your health care provider if you have any questions or need more information.

HOW TO APPLY

Apply Targretin gel to your CTCL lesions using a clean washed finger. Place a generous coating of gel over the entire surface of each lesion. You should not apply gel to the healthy skin around the lesion. The extra effort you take in carefully applying the gel only to the area of the CTCL lesion will help to lessen any irritation or redness that may occur. Proper application should leave some gel visible on the surface of the lesion when you are finished with the application.

Immediately following application, wipe the finger(s) you have used to apply the gel with a disposable tissue and wash your hands using soap and water.

Allow five (5) to ten (10) minutes for the gel to dry before covering a treated area with clothing.

A mild non-deodorant soap is recommended when bathing or showering. If you apply Targretin gel after your shower or bath, you should wait 20 minutes before application.

WHEN TO APPLY

Targretin gel should be applied at an initial frequency of once every other day for the first week. The frequency of application should then be increased as tolerated at weekly intervals to once daily, then twice daily, then three times daily, and finally four times daily. Your health care provider may instruct you to apply Targretin gel at a different frequency.

YOU SHOULD AVOID. . .

You should avoid applying Targretin gel to areas of healthy skin around a CTCL lesion. Exposure of healthy skin to Targretin gel may cause unnecessary irritation or redness.

You should avoid showering, bathing, or swimming until at least three (3) hours after any application, if possible.

You should avoid covering the CTCL lesions treated with Targretin gel with any bandage or material other than loose clothing.

You should avoid prolonged exposure of the treated area to sunlight or other ultraviolet (UV) light (such as tanning lamps).

You should avoid the use of other topical products on your treated CTCL lesions.

You should avoid scratching the treated areas.

WHAT SIDE EFFECTS DOES TARGRETIN GEL HAVE?

While using Targretin gel, you may experience some local effects such as redness, itching, burning, irritation, and scaling at the area of application. In clinical trials, the majority of these effects were mild or moderate, but some patients did experience more severe rash, itching, irritation, and inflammation. A few patients discontinued treatment due to these types of effects. Should these or other effects become troublesome to you, consult your health care provider. He or she can provide information on how to manage these effects.

All medications have side effects. You should call your physician regarding any questions or concerns you may have when using Targretin gel.

HOW QUICKLY CAN I EXPECT TARGRETIN GEL TO WORK?

Be patient. Targretin gel takes time to work. In clinical trials, some patients began to respond as early as 4 weeks, but most patients did not experience their best response until 48 to 62 weeks of treatment. Do not stop treatment at the first sign of improvement. Continue to use Targretin gel as instructed by your health care provider.

OTHER INFORMATION

The opening of the Targretin gel tube is covered by a metal safety seal. If this seal has been punctured or is not visible when you first open the package, DO NOT USE this tube and promptly return the product to your pharmacy or place of purchase.

To open, use the pointed portion of the cap to puncture the metal safety seal.

Always use the cap to close the tube tightly after each use.

Store at room temperature. Keep away from heat or flame.

The gel should not be used after the expiration date printed on the tube.

Keep this medicine out of the reach and sight of children.

IF YOU HAVE QUESTIONS. . . .

If you have questions about your treatment, talk with your health care provider.

All other product/brand names are trademarks of their respective owners.

Distributed by:
Bausch Health US, LLC
Bridgewater, NJ 08807 USA

Manufactured by:
DPT Laboratories, Ltd.
San Antonio, TX 78215 USA

Targretin is a trademark of Bausch Health Companies Inc. or its affiliates.

© 2020 Bausch Health Companies Inc. or its affiliates

Rev. 02/2020

9553902

PACKAGE LABEL

PRINCIPAL DISPLAY PANEL - Carton 60 grams

NDC 0187-5525-60

Rx only

Targretin®
(bexarotene) 1% gel

Net Wt. 60 grams

Not for Ophthalmic Use

For Topical Use Only

Ortho Dermatologics